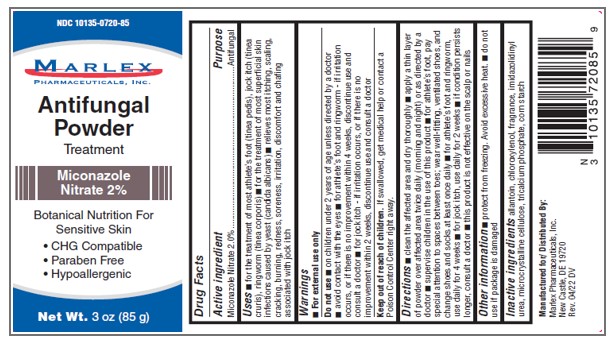 DRUG LABEL: Miconazole Nitrate Antifungal Powder
NDC: 10135-720 | Form: POWDER
Manufacturer: Marlex Pharmaceuticals, Inc.
Category: otc | Type: HUMAN OTC DRUG LABEL
Date: 20251121

ACTIVE INGREDIENTS: MICONAZOLE NITRATE 2 g/100 g
INACTIVE INGREDIENTS: CHLOROXYLENOL; IMIDUREA; MICROCRYSTALLINE CELLULOSE; TRICALCIUM PHOSPHATE; ALLANTOIN; STARCH, CORN

Active ingredient

Miconazole Nitrate 2%

Purpose

Antifungal

Uses

- For the treatment of most athlete's foot (tinea pedis), jock itch (tinea cruris), ringworm (tinea corporis)
- For the treatment of most superficial skin infections caused by yeast (candida albicans)
- Relieves most itching, scaling, cracking, burning, redness, soreness, irritation, discomfort and chafing associated with jock itch

Warnings

- For external use only

Do not use

- on children under 2 years of age unless directed by a doctor
- avoid contact with the eyes
- for athlete's foot and ringworm- if irritation occurs, or if there is no improvement within 4 weeks, discontinue use and consult a doctor
- for jock itch - if irritation occurs or if there is no improvement within 2 weeks, discontinue use and consult a doctor

Keep out of reach of children

If swallowed, get medical help or contact a Poison Control center right away.

Directions

- Clean the affected area and dry thoroughly
- Apply a layer of power over affected area twice a day (morning and night) or as directed by a doctor
- Supervise children in the use of this product

For athlete's foot, pay special attention to spaces between toes; wear well fitting, ventilated shoes, and change shoes and socks at least once daily

- For athlete's foot and ringworm, use daily for 4 weeks
- For jock itch, use daily for 2 weeks
- If condition persists longer, consult a doctor
- This product is not effective on the scalp or nails.

Other Information

- Protect from freezing. Avoid excessive heat.
- Do not use if package is damaged

Inactive ingredients

Allantoin, Chloroxylenol, fragrance, Imidazolidinyl Urea, Microcrystalline Cellulose, Tricalcium Phosphate, Corn starch.

Manufactured For/ Distributed By:

Marlex Pharmaceuticals, Inc.

New Castle, DE 19720

Rev. 04/22 DV